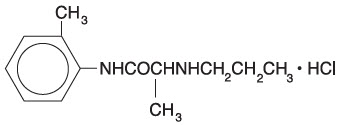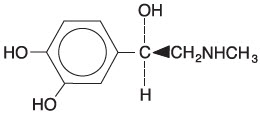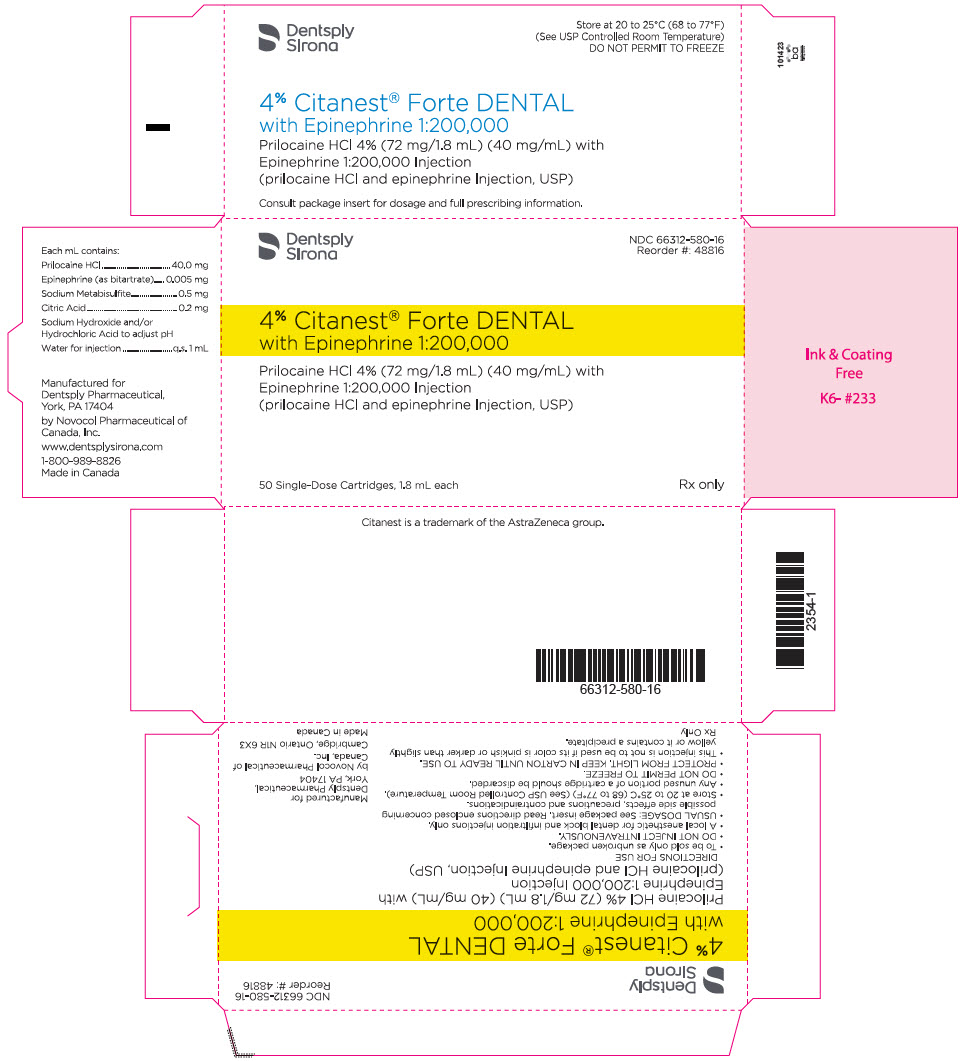 DRUG LABEL: Citanest Forte DENTAL
NDC: 66312-580 | Form: INJECTION, SOLUTION
Manufacturer: Dentsply Pharmaceutical Inc.
Category: prescription | Type: HUMAN PRESCRIPTION DRUG LABEL
Date: 20240229

ACTIVE INGREDIENTS: PRILOCAINE HYDROCHLORIDE 40 mg/1 mL; EPINEPHRINE BITARTRATE 0.005 mg/1 mL
INACTIVE INGREDIENTS: SODIUM HYDROXIDE; WATER; SODIUM METABISULFITE 0.5 mg/1 mL; HYDROCHLORIC ACID; ANHYDROUS CITRIC ACID 0.2 mg/1 mL

4% Citanest® Forte DENTAL with Epinephrine 1:200,000
Prilocaine HCl 4% (72 mg/1.8 mL) (40 mg/mL) with Epinephrine 1:200,000 Injection
(prilocaine HCl and epinephrine injection, USP)

For Local Anesthesia in Dentistry

Rx Only

DESCRIPTION

4% Citanest® Forte DENTAL with Epinephrine 1:200,000 (Citanest Forte), Prilocaine HCl 4% (72 mg/1.8 mL) (40 mg/mL) with Epinephrine 1:200,000 Injection, is a sterile, non-pyrogenic isotonic solution that contains a local anesthetic agent with epinephrine (as bitartrate) and is administered parenterally by injection. See INDICATIONS AND USAGE for specific uses. The quantitative composition is shown in Table 1.

Citanest Forte contains prilocaine HCl, which is chemically designated as propanamide, N-(2-methyl-phenyl) -2- (propylamino)-, monohydrochloride and has the following structural formula:

C13H20N2O ∙ HCl molecular wt = 256.77

and epinephrine, which is (-) -3, 4-Dihydroxy- ∝ -[(methylamino) methyl] benzyl alcohol and has the following structural formula:

C9H13NO3 molecular wt = 183.21

Parenteral drug products should be inspected visually for particulate matter and discoloration prior to administration.

The specific quantitative composition is shown in Table 1.

Table 1. COMPOSITION
Product Identification | Formula (mg/mL)
Product Identification | Prilocaine HCl | Epinephrine (as bitartrate) | Citric Acid | Sodium Metabisulfite | pH
4% Citanest® Forte DENTAL with Epinephrine 1:200,000 (Prilocaine HCl 4% (72 mg/1.8 mL) (40 mg/mL) with Epinephrine 1:200,000 Injection) | 40.0 | 0.005 | 0.2 | 0.5 | 3.3 to 5.5
Note: Sodium hydroxide and/or hydrochloric acid may be used to adjust the pH of Citanest Forte.

CLINICAL PHARMACOLOGY

Mechanism of Action

Prilocaine stabilizes the neuronal membrane by inhibiting the ionic fluxes required for the initiation and conduction of impulses, thereby effecting local anesthetic action.

Onset and Duration of Action

When used for infiltration injection in dental patients, the time of onset of anesthesia averages less than 2 minutes with an average duration of soft tissue anesthesia of approximately 2¼ hours.

When used for inferior alveolar nerve block, the time of onset averages less than three minutes with an average duration of soft tissue anesthesia of approximately 3 hours.

Hemodynamics

Excessive blood levels may cause changes in cardiac output, total peripheral resistance, and mean arterial pressure.

These changes may be attributable to a direct depressant effect of the local anesthetic agent on various components of the cardiovascular system and/or the beta-adrenergic receptor stimulating action of epinephrine.

Pharmacokinetics and Metabolism

Information derived from diverse formulations, concentrations and usages reveals that prilocaine is completely absorbed following parenteral administration, its rate of absorption depending, for example, upon such factors as the site of administration and the presence or absence of a vasoconstrictor agent. Prilocaine is metabolized in both the liver and the kidney and excreted via the kidney. It is not metabolized by plasma esterases. Hydrolysis of prilocaine by amidases yields ortho-toluidine and n-proylalanine. Both of these compounds may undergo ring hydroxylation.

O-toluidine has been found to produce methemoglobin, both in vitro and in vivo (see ADVERSE REACTIONS).

Because prilocaine is metabolized in both the liver and kidneys, hepatic and renal dysfunction may alter prilocaine kinetics.

As with other local anesthetic agents, the plasma binding of prilocaine may be dependent on drug concentration. At 0.5 to 1.0 mg/mL it is 55% protein bound.

Prilocaine crosses the blood-brain and placental barriers, presumably by passive diffusion.

Factors such as acidosis and the use of CNS stimulants and depressants affect the CNS levels of prilocaine required to produce overt systemic effects. In the rhesus monkey, arterial blood levels of 20 mg/mL have been shown to be the threshold for convulsive activity.

INDICATIONS AND USAGE

Citanest Forte is indicated for the production of local anesthesia in dentistry by nerve block or infiltration techniques. Only accepted procedures for these techniques as described in standard textbooks are recommended.

CONTRAINDICATIONS

Prilocaine is contraindicated in patients with a known history of hypersensitivity to local anesthetics of the amide type and in those rare patients with congenital or idiopathic methemoglobinemia.

WARNINGS

DENTAL PRACTITIONERS WHO EMPLOY LOCAL ANESTHETIC AGENTS SHOULD BE WELL VERSED IN DIAGNOSIS AND MANAGEMENT OF EMERGENCIES THAT MAY ARISE FROM THEIR USE. RESUSCITATIVE EQUIPMENT, OXYGEN AND OTHER RESUSCITATIVE DRUGS SHOULD BE AVAILABLE FOR IMMEDIATE USE.

Methemoglobinemia

Cases of methemoglobinemia have been reported in association with local anesthetic use. Although all patients are at risk for methemoglobinemia, patients with glucose-6-phosphate dehydrogenase deficiency, congenital or idiopathic methemoglobinemia, cardiac or pulmonary compromise, infants under 6 months of age, and concurrent exposure to oxidizing agents or their metabolites are more susceptible to developing clinical manifestations of the condition. If local anesthetics must be used in these patients, close monitoring for symptoms and signs of methemoglobinemia is recommended.

Signs of methemoglobinemia may occur immediately or may be delayed some hours after exposure, and are characterized by a cyanotic skin discoloration and/or abnormal coloration of the blood. Methemoglobin levels may continue to rise; therefore, immediate treatment is required to avert more serious central nervous system and cardiovascular adverse effects, including seizures, coma, arrhythmias, and death. Discontinue CITANEST FORTE and any other oxidizing agents. Depending on the severity of the signs and symptoms, patients may respond to supportive care, i.e., oxygen therapy, hydration. A more severe clinical presentation may require treatment with methylene blue exchange transfusion, or hyperbaric oxygen.

To minimize the likelihood of intravascular injection, aspiration should be performed before the local anesthetic solution is injected. If blood is aspirated, the needle must be repositioned until no return of blood can be elicited by aspiration. Note, however, that the absence of blood in the syringe does not assure that intravascular injection will be avoided.

Citanest Forte contains sodium metabisulfite, a sulfite that may cause allergic-type reactions including anaphylactic symptoms and life-threatening or less severe asthmatic episodes in certain susceptible people. The overall prevalence of sulfite sensitivity in the general population is unknown and probably low. Sulfite sensitivity is seen more frequently in asthmatic than non-asthmatic people.

PRECAUTIONS

General

The safety and effectiveness of prilocaine depend on proper dosage, correct technique, adequate precautions, and readiness for emergencies. Standard textbooks should be consulted for specific techniques and precautions for various regional anesthetic procedures. Resuscitative equipment, oxygen, and other resuscitative drugs should be available for immediate use. (See WARNINGS and ADVERSE REACTIONS.) The lowest dosage that results in effective anesthesia should be used to avoid high plasma levels and serious adverse effects. Repeated doses of prilocaine may cause significant increases in blood levels with each repeated dose because of slow accumulation of the drug or its metabolites. Tolerance to elevated blood levels varies with the status of the patient. Debilitated, elderly patients, acutely ill patients, and children should be given reduced doses commensurate with their age and physical status. Prilocaine should also be used with caution in patients with severe shock or heart block.

Local anesthetic injections containing a vasoconstrictor should be used cautiously in areas of the body supplied by end arteries or having otherwise compromised blood supply. Patients with peripheral vascular disease and those with hypertensive vascular disease may exhibit exaggerated vasoconstrictor response. Ischemic injury or necrosis may result. Preparations containing a vasoconstrictor should be used with caution in patients during or following the administration of potent general anesthetic agents, since cardiac arrhythmias may occur under such conditions.

Cardiovascular and respiratory (adequacy of ventilation) vital signs and the patient's state of consciousness should be monitored after each local anesthetic injection. Restlessness, anxiety, tinnitus, dizziness, blurred vision, tremors, depression or drowsiness should alert the practitioner to the possibility of central nervous system toxicity. Signs and symptoms of depressed cardiovascular function may commonly result from a vasovagal reaction, particularly if the patient is in an upright position. (See ADVERSE REACTIONS, Cardiovascular System).

Since amide-type local anesthetics are metabolized by the liver, prilocaine should be used with caution in patients with hepatic disease.

Patients with severe hepatic disease, because of their inability to metabolize local anesthetics normally, are at greater risk of developing toxic plasma concentrations. Prilocaine should also be used with caution in patients with impaired cardiovascular function since they may be less able to compensate for functional changes associated with the prolongation of A-V conduction produced by these drugs.

Many drugs used during the conduct of anesthesia are considered potential triggering agents for familial malignant hyperthermia. Since is not known whether amide-type local anesthetics may trigger this reaction and since the need for supplemental general anesthesia cannot be predicted in advance, it is suggested that a standard protocol for the management of malignant hyperthermia should be available. Early unexplained signs of tachycardia, tachypnea, labile blood pressure and metabolic acidosis may precede temperature elevation. Successful outcome is dependent on early diagnosis, prompt discontinuance of the suspect triggering agent(s) and institution of treatment, including oxygen therapy, indicated supportive measures and dantrolene (consult dantrolene sodium intravenous package insert before using).

Prilocaine should be used with caution in persons with known drug sensitivities. Patients allergic to para-aminobenzoic acid derivatives (procaine, tetracaine, benzocaine, etc.) have not shown cross sensitivity to prilocaine.

Use in the Head and Neck Area

Small doses of local anesthetics injected into the head and neck area, including retrobulbar, dental and stellate ganglion blocks, may produce adverse reactions similar to systemic toxicity seen with unintentional intravascular injections of larger doses. Confusion, convulsions, respiratory depression and/or respiratory arrest, and cardiovascular stimulation or depression have been reported. These reactions may be due to intra-arterial injection of the local anesthetic with retrograde flow to the cerebral circulation. Patients receiving these blocks should have their circulation and respiration monitored and be constantly observed. Resuscitative equipment and personnel for treating adverse reactions should be immediately available. Dosage recommendations should not be exceeded. (See DOSAGE AND ADMINISTRATION.)

Information for Patients

Inform patients that use of local anesthetics may cause methemoglobinemia, a serious condition that must be treated promptly. Advise patients or caregivers to seek immediate medical attention if they or someone in their care experience the following signs or symptoms: pale, gray, or blue colored skin (cyanosis); headache; rapid heart rate; shortness of breath; lightheadedness; or fatigue.

The patient should be informed of the possibility of temporary loss of sensation and muscle function following infiltration or nerve block injections.

The patient should be advised to exert caution to avoid inadvertent trauma to the lips, tongue, cheek mucosae or soft palate when these structures are anesthetized. The ingestion of food should therefore be postponed until normal function returns.

The patient should be advised to consult the dentist if anesthesia persists, or if a rash develops.

Clinically Significant Drug Interactions

Patients who are administered local anesthetics are at increased risk of developing methemoglobinemia when concurrently exposed to the following drugs, which could include other local anesthetics:

EXAMPLES OF DRUGS ASSOCIATED WITH METHEMOGLOBINEMIA:
Class | Examples
Nitrates/Nitrites | nitric oxide, nitroglycerin, nitroprusside, nitrous oxide
Local anesthetics | articaine, benzocaine, bupivacaine, lidocaine, mepivacaine, prilocaine, procaine, ropivacaine, tetracaine
Antineoplastic Agents | cyclophosphamide, flutamide, hydroxyurea, ifosfamide, rasburicase
Antibiotics | dapsone, nitrofurantoin, para-aminosalicylic acid, sulfonamides
Antimalarials | chloroquine, primaquine
Anticonvulsants | phenobarbital, phenytoin, sodium valproate
Other drugs | acetaminophen, metoclopramide, quinine, sulfasalazine

The administration of local anesthetic injections containing epinephrine or norepinephrine to patients receiving monoamine oxidase inhibitors, tricyclic antidepressants or phenothiazines may produce severe, prolonged hypotension or hypertension. Concurrent use of these agents should generally be avoided. In situations when concurrent therapy is necessary, careful patient monitoring is essential.

Concurrent administration of vasopressor drugs and ergot-type oxytocic drugs may cause severe, persistent hypertension or cerebrovascular accidents.

Drug/Laboratory Test Interactions

The intramuscular injection of prilocaine may result in an increase in creatine phosphokinase levels. Thus, the use of this enzyme determination, without isoenzyme separation, as a diagnostic test for the presence of acute myocardial infarction may be compromised by the intramuscular injection of prilocaine.

Carcinogenesis, Mutagenesis, Impairment of Fertility

Studies of prilocaine in animals to evaluate the carcinogenic and mutagenic potential or the effect on fertility have not been conducted.

Chronic oral toxicity studies of ortho-toluidine, a metabolite of prilocaine, in mice (150 to 4800 mg/kg) and rats (150 to 800 mg/kg) have shown that ortho-toluidine is a carcinogen in both species. The lowest dose corresponds to approximately 50 times the maximum amount of ortho-toluidine to which a 50 kg subject would be expected to be exposed following a single injection (8 mg/kg) of prilocaine.

Ortho-toluidine (0.5 mg/mL) showed positive results in Escherichia coli DNA repair and phage-induction assays. Urine concentrates from rats treated with ortho-toluidine (300 mg/kg, orally) were mutagenic for Salmonella typhimurium with metabolic activation. Several other tests, including reverse mutations in five different Salmonella typhimurium strains with or without metabolic activation and single strand breaks in DNA of V79 Chinese hamster cells, were negative.

Use in Pregnancy

Teratogenic Effects

Pregnancy Category B

Reproduction studies have been performed in rats at doses up to 30 times the human dose and revealed no evidence of impaired fertility or harm to the fetus due to prilocaine. There are, however, no adequate and well-controlled studies in pregnant women. Animal reproduction studies are not always predictive of human response. General consideration should be given to this fact before administering prilocaine to women of childbearing potential, especially during early pregnancy when maximum organogenesis takes place.

Nursing Mothers

It is not known whether this drug is excreted in human milk. Because many drugs are excreted in human milk, caution should be exercised when prilocaine is administered to a nursing woman.

Pediatric Use

Dosages in children should be reduced, commensurate with age, body weight, and physical condition. (See DOSAGE AND ADMINISTRATION.)

ADVERSE REACTIONS

Swelling and persistent paresthesia of the lips and oral tissues may occur. Persistent paresthesia lasting weeks to months, and in rare instances paresthesia lasting greater than one year have been reported.

Adverse experiences following the administration of prilocaine are similar in nature to those observed with other amide local anesthetic agents. These adverse experiences are, in general, dose-related and may result from high plasma levels caused by excessive dosage, rapid absorption or unintentional intravascular injection, or may result from a hypersensitivity, idiosyncrasy or diminished tolerance on the part of the patient. Serious adverse experiences are generally systemic in nature. The following types are those most commonly reported:

Central Nervous System

CNS manifestations are excitatory and/or depressant and may be characterized by lightheadedness, nervousness, apprehension, euphoria, confusion, dizziness, drowsiness, tinnitus, blurred or double vision, vomiting, sensations of heat, cold or numbness, twitching, tremors, convulsions, unconsciousness, respiratory depression, and arrest. The excitatory manifestations may be very brief or may not occur at all, in which case the first manifestation of toxicity may be drowsiness merging into unconsciousness and respiratory arrest.

Drowsiness following the administration of prilocaine is usually an early sign of a high blood level of the drug and may occur as a consequence of rapid absorption.

Cardiovascular System

Cardiovascular manifestations are usually depressant and are characterized by bradycardia, hypotension, and cardiovascular collapse, which may lead to cardiac arrest.

Signs and symptoms of depressed cardiovascular function may commonly result from a vasovagal reaction, particularly if the patient is in an upright position. Less commonly, they may result from a direct effect of the drug. Failure to recognize the premonitory signs such as sweating, a feeling of faintness, and changes in pulse or sensorium may result in progressive cerebral hypoxia and seizure or serious cardiovascular catastrophe. Management consists of placing the patient in the recumbent position and ventilation with oxygen. Supportive treatment of circulatory depression may require the administration of intravenous fluids, and, when appropriate, a vasopressor (e.g., ephedrine) as directed by the clinical situation.

Allergic

Allergic reactions are characterized by cutaneous lesions, urticaria, edema or anaphylactoid reactions. Allergic reactions as a result of sensitivity to prilocaine are extremely rare and, if they occur, should be managed by conventional means. The detection of sensitivity by skin testing is of doubtful value.

Neurologic

The incidences of adverse reactions (e.g., persistent neurologic deficit) associated with the use of local anesthetics may be related to the technique employed, the total dose of local anesthetic administered, the particular drug used, the route of administration, and the physical condition of the patient.

OVERDOSAGE

Acute emergencies from local anesthetics are generally related to high plasma levels encountered during therapeutic use of local anesthetics (see ADVERSE REACTIONS, WARNINGS, and PRECAUTIONS).

Management of Local Anesthetic Emergencies

The first consideration is prevention, best accomplished by careful and constant monitoring of cardiovascular and respiratory vital signs and the patient's state of consciousness after each local anesthetic injection. At the first sign of change, oxygen should be administered.

The first step in the management of convulsions consists of immediate attention to the maintenance of a patent airway and assisted or controlled ventilation with oxygen and a delivery system capable of permitting immediate positive airway pressure by mask. Immediately after the institution of these ventilatory measures, the adequacy of the circulation should be evaluated, keeping in mind that drugs used to treat convulsions sometimes depress the circulation when administered intravenously. Should convulsions persist despite adequate respiratory support, and if the status of the circulation permits, small increments of an ultra-short acting barbiturate (such as thiopental or thiamylal) or a benzodiazepine (such as diazepam) may be administered intravenously. The clinician should be familiar, prior to use of local anesthetics, with these anticonvulsant drugs. Supportive treatment of circulatory depression may require administration of intravenous fluids and, when appropriate, a vasopressor as directed by the clinical situation (e.g., ephedrine).

If not treated immediately, both convulsions and cardiovascular depression can result in hypoxia, acidosis, bradycardia, arrhythmias and cardiac arrest. If cardiac arrest should occur, standard cardiopulmonary resuscitative measures should be instituted.

Endotracheal intubation, employing drugs and techniques familiar to the clinician, may be indicated, after initial administration of oxygen by mask, if difficulty is encountered in the maintenance of a patent airway or if prolonged ventilatory support (assisted or controlled) is indicated.

Dialysis is of negligible value in the treatment of acute overdosage with prilocaine.

The development of methemoglobinemia is generally dose related but may occur at any dose in susceptible individuals. While methemoglobin values of less than 20% do not generally produce any clinical symptoms, the appearance of cyanosis at 2 to 4 hours following administration should be evaluated in terms of the general health status of the patient.

Methemoglobinemia can be reversed when indicated by intravenous administration of methylene blue at a dosage of 1 to 2 mg/kg given over a five minute period.

The subcutaneous LD50 of prilocaine HCl in female mice is 550 (359 to 905) mg/kg.

DOSAGE AND ADMINISTRATION

The dosage of Citanest Forte varies and depends on the physical status of the patient, the area of the oral cavity to be anesthetized, the vascularity of the oral tissues, and the technique of anesthesia. The least volume of injection that results in effective local anesthesia should be administered. For specific techniques and procedures of local anesthesia in the oral cavity, refer to standard textbooks.

Inferior Alveolar Block

There are no practical clinical differences between prilocaine with and without epinephrine when used for inferior alveolar blocks.

Maxillary Infiltration

4% Citanest Plain (without epinephrine) is recommended for use in maxillary infiltration anesthesia for procedures in which the painful aspects can be completed within 15 minutes after the injection. 4% Citanest Plain is therefore especially suited to short procedures in the maxillary anterior teeth. For long procedures, or those involving maxillary posterior teeth where soft tissue numbness is not troublesome to the patient, Citanest Forte is recommended.

For most routine procedures, initial dosages of 1 to 2 mL of Citanest Forte will usually provide adequate infiltration or major nerve block anesthesia.

The maximum recommended dose that should ever be administered within a two hour period in normal healthy adults should be calculated based upon the patient's weight as follows:

Weight | Maximum recommended dose
<150 lb (<70 kg) | 4 mg/lb (8mg/kg)
≥ 150 lb (≥ 70 kg) | 600 mg (15 mL) or 8 cartridges

In children under 10 years of age it is rarely necessary to administer more than one-half cartridge (40 mg) of Citanest Forte per procedure to achieve local anesthesia for a procedure involving a single tooth. In maxillary infiltration, this amount will often suffice to the treatment of two or even three teeth. In the mandibular block, however, satisfactory anesthesia achieved with this amount of drug will allow treatment of the teeth in an entire quadrant.

ASPIRATION PRIOR TO INJECTION IS RECOMMENDED, since it reduces the possibility of intravascular injection, thereby keeping the incidence of side effects and anesthetic failure to a minimum.

NOTE: Parenteral drug products should be inspected visually for particulate matter and discoloration prior to administration whenever the solution and container permit. Solutions that are discolored and/or contain particulate matter should not be used.

Any unused portion of a cartridge should be discarded.

Maximum Recommended Dosages

In patients weighing <150 lb (70 kg), no more than 4 mg/lb (8 mg/kg) should be administered. In patients weighing ≥150 lb, no more than 600 mg (8 cartridges) of prilocaine HCl should be administered as a single injection.

Children

It is difficult to recommend a maximum dose of any drug for children since this varies as a function of age and weight. For children of less than ten years who have a normal lean body mass and normal body development, the maximum dose may be determined by the application of one of the standard pediatric drug formulas (e.g., Clark's rule). For example, in a child of five years weighing 50 lb, the dose of prilocaine HCl should not exceed 150 to 200 mg (6.6 to 8.8 mg/kg or 3 to 4 mg/lb of body weight) when calculated according to Clark's rule.

HOW SUPPLIED

Citanest Forte (NDC 66312-580-16) is dispensed in 1.8 mL single-dose cartridges, packed 50 per box.

Sterilization, Storage and Technical Procedures:

1. Cartridges should not be autoclaved, because solutions of epinephrine and the closures employed in cartridges cannot withstand autoclaving temperatures and pressures.
2. If chemical disinfection of anesthetic cartridges is desired, either 91% isopropyl alcohol or 70% ethyl alcohol is recommended. Many commercially available brands of rubbing alcohol, as well as solutions of ethyl alcohol not of U.S.P. grade, contain denaturants that are injurious to rubber and, therefore, are not to be used. It is recommended that chemical disinfection be accomplished by wiping the cartridge cap thoroughly with a pledget of cotton that has been moistened with the recommended alcohol just prior to use. IMMERSION IS NOT RECOMMENDED.
3. Certain metallic ions (mercury, zinc, copper, etc.) have been related to swelling and edema after local anesthesia in dentistry. Therefore, chemical disinfectants containing or releasing those ions are not recommended. Antirust tablets usually contain metal ions. Accordingly, aluminum sealed cartridges should not be kept in such solutions.
4. Quaternary ammonium salts, such as benzalkonium chloride, are electrolytically incompatible with aluminum. Cartridges are sealed with aluminum caps and therefore should not be immersed in any solution containing these salts.
5. To avoid leakage of solutions during injection, be sure to penetrate the center of the rubber diaphragm when loading the syringe. An off-center penetration produces an oval shaped puncture that allows leakage around the needle.
  Other causes of leakage and breakage include badly worn syringes, aspirating syringes with bent harpoons, the use of syringes not designed to take 1.8 mL cartridges, and inadvertent freezing.
6. Cracking of glass cartridges is most often the result of an attempt to use a cartridge with an extruded plunger. An extruded plunger loses its lubrication and can be forced back into the cartridge only with difficulty. Cartridges with extruded plungers should be discarded.
7. Store at 20° to 25°C (68° to 77°F); excursions permitted between 15° to 30°C (59° to 86°F) [see USP Controlled Room Temperature].
8. Solutions containing epinephrine should be protected from light.

Manufactured for
Dentsply Pharmaceutical,
York, PA 17404
by Novocol Pharmaceutical of Canada, Inc

Dentsply
Sirona

Rev 08/2020 (2353-2)

PRINCIPAL DISPLAY PANEL - 50 Cartridge Carton

Dentsply
Sirona
NDC 66312-580-16
Reorder #: 48816

4% Citanest® Forte DENTAL
with Epinephrine 1:200,000

Prilocaine HCl 4% (72 mg/1.8 mL) (40 mg/mL) with
Epinephrine 1:200,000 Injection
(prilocaine HCl and epinephrine Injection, USP)

50 Single-Dose Cartridges, 1.8 mL each
Rx only